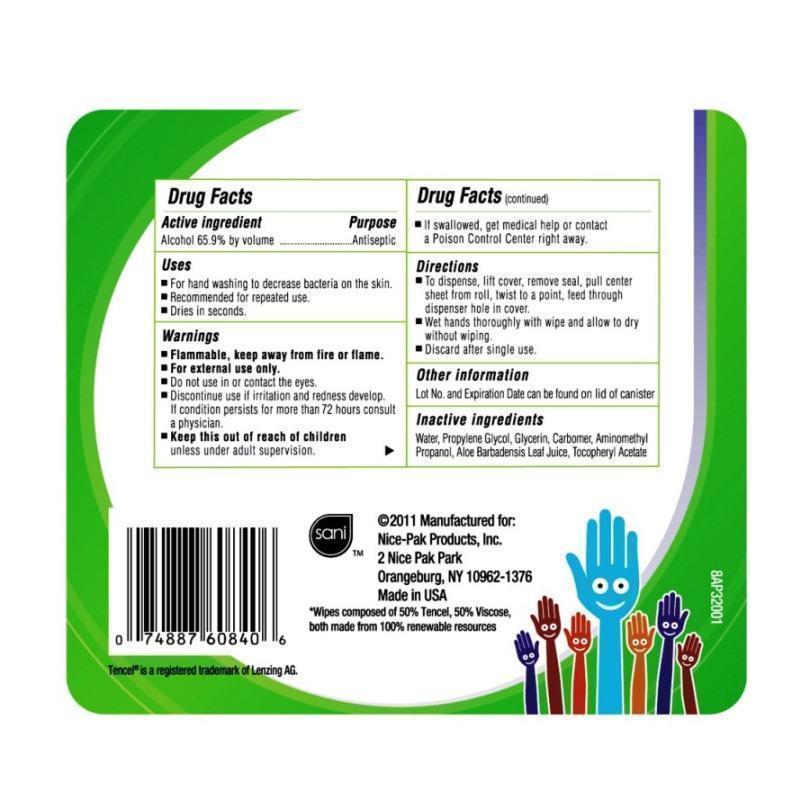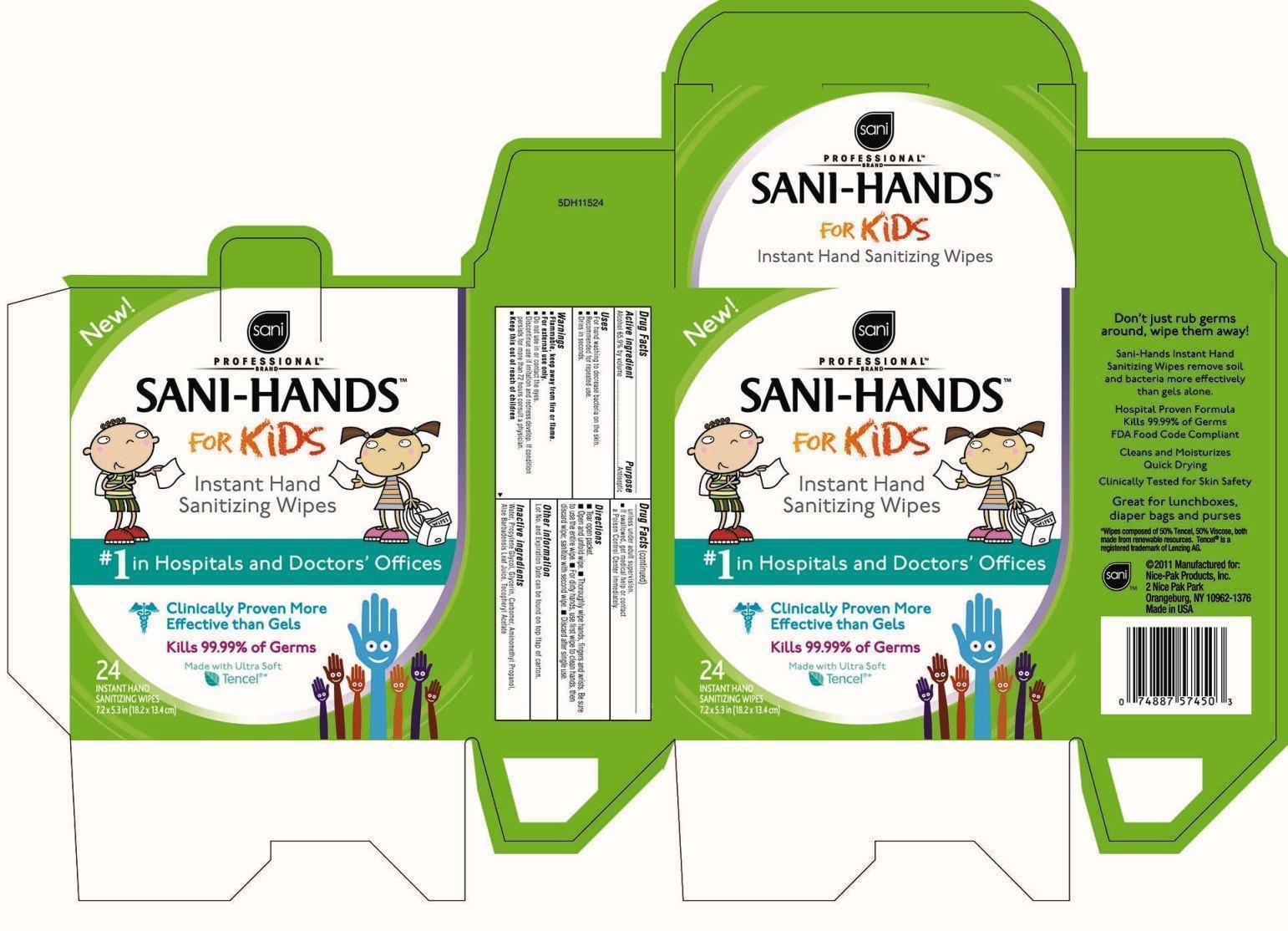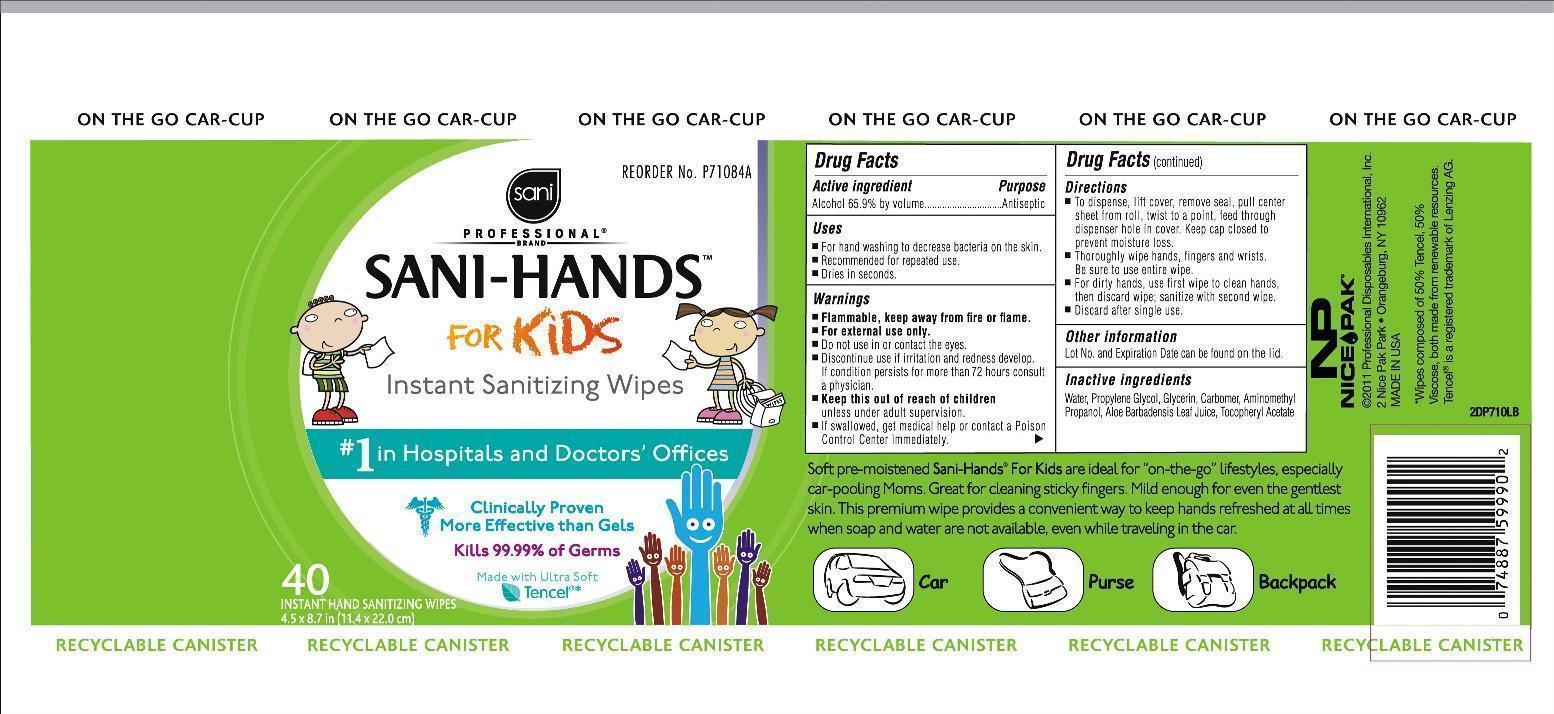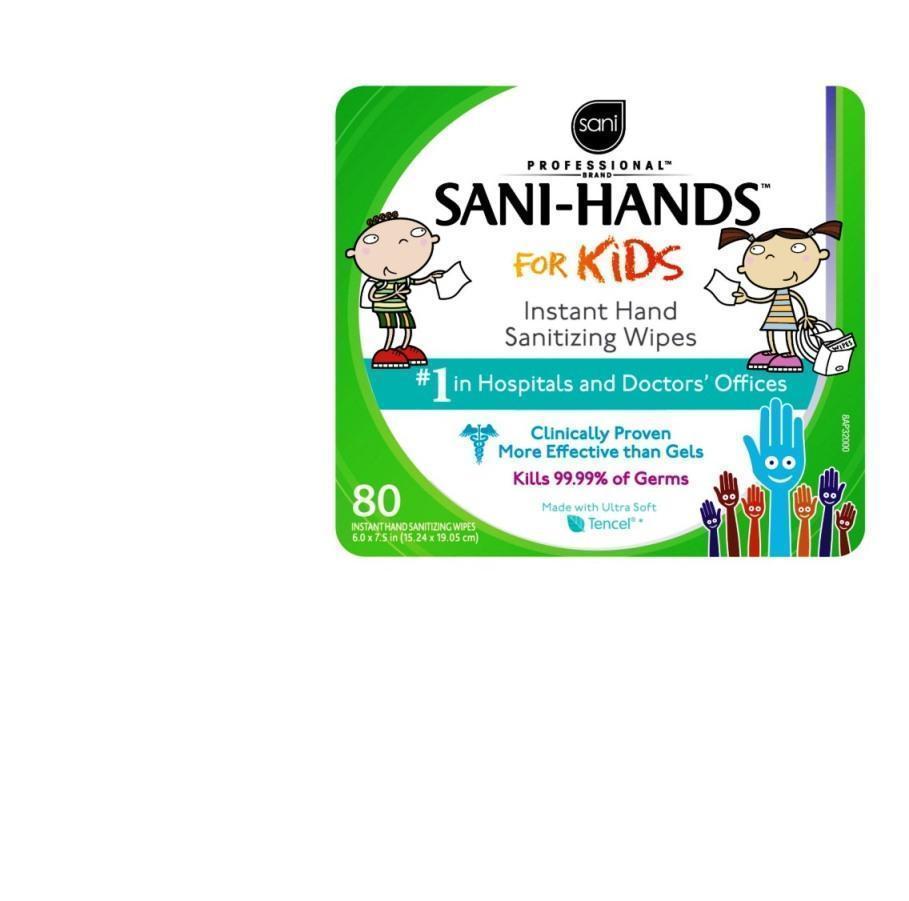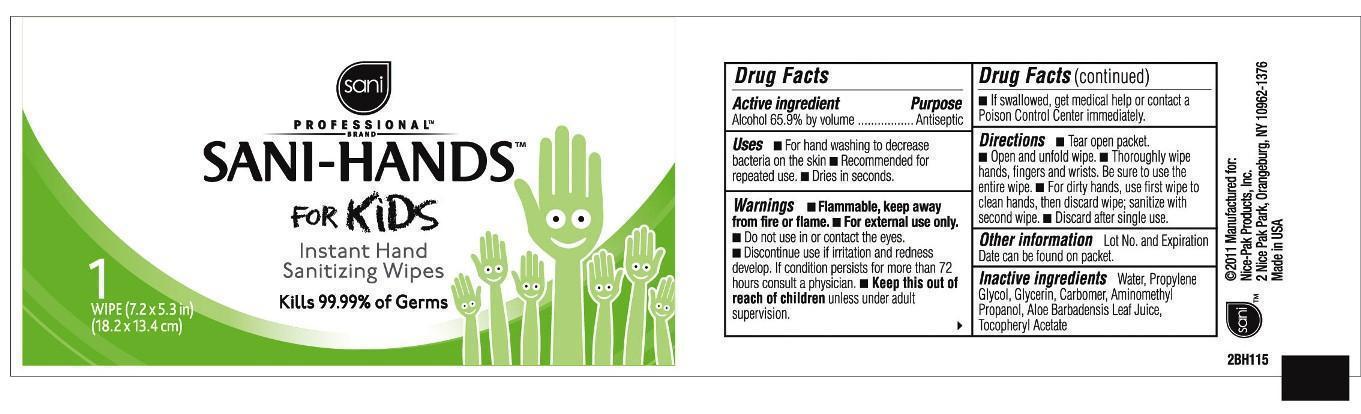 DRUG LABEL: Sani Professional Brand Sani-Hands for Kids
NDC: 10819-7004 | Form: CLOTH
Manufacturer: Professional Disposables International, Inc.
Category: otc | Type: HUMAN OTC DRUG LABEL
Date: 20251110

ACTIVE INGREDIENTS: ALCOHOL 0.659 mL/1 mL
INACTIVE INGREDIENTS: WATER; PROPYLENE GLYCOL; GLYCERIN; CARBOMER HOMOPOLYMER TYPE C; AMINOMETHYL PROPANEDIOL; ALOE VERA LEAF; ALPHA-TOCOPHEROL ACETATE

Drug Facts

INDICATIONS AND USAGE

- For hand washing to decrease bacteria on the skin.
- Recommended for repeated use.
- Dries in seconds

WARNINGS

- Flammable, keep away from fire or flame.
- For external use only.
- Do not use in or contact the eyes.
- Discontinue use if irritation and redness develop. If condition persist for more than 72 hours consult a physician.
- If swallowed, get medical help or contact a Poison Control Center immediately.

KEEP OUT OF REACH OF CHILDREN

- Keep this out of reach of childrenunless under adult supervision.

Lot No. and Expiration Date can be found on the lid.

Dosage

For dirty hands, use first wipe to clean hands, then discard wipe; sanitize with second wipe. Discard after single use.

INACTIVE INGREDIENT

Water, Propylene Glycol, Glycerin, Carbomer, Aminometyl Propanol, Aloe Barbadensis Leaf Juice, Tocopheryl Acetate

(C) 2011 Manufactured for: PDII/Nice-Pak Products, Inc.
2 Nice-Pak Park, Orangeburg, NY 10962-1376 Made in USA

*Wipes composed of 50% Tencel, 50% Viscose, both made from renewable resources.

Tencel(R)is a registered trademark of Lenzing AG.

ACTIVE INGREDIENT

Alcohol 65.9% by volume

PURPOSE

Antiseptic